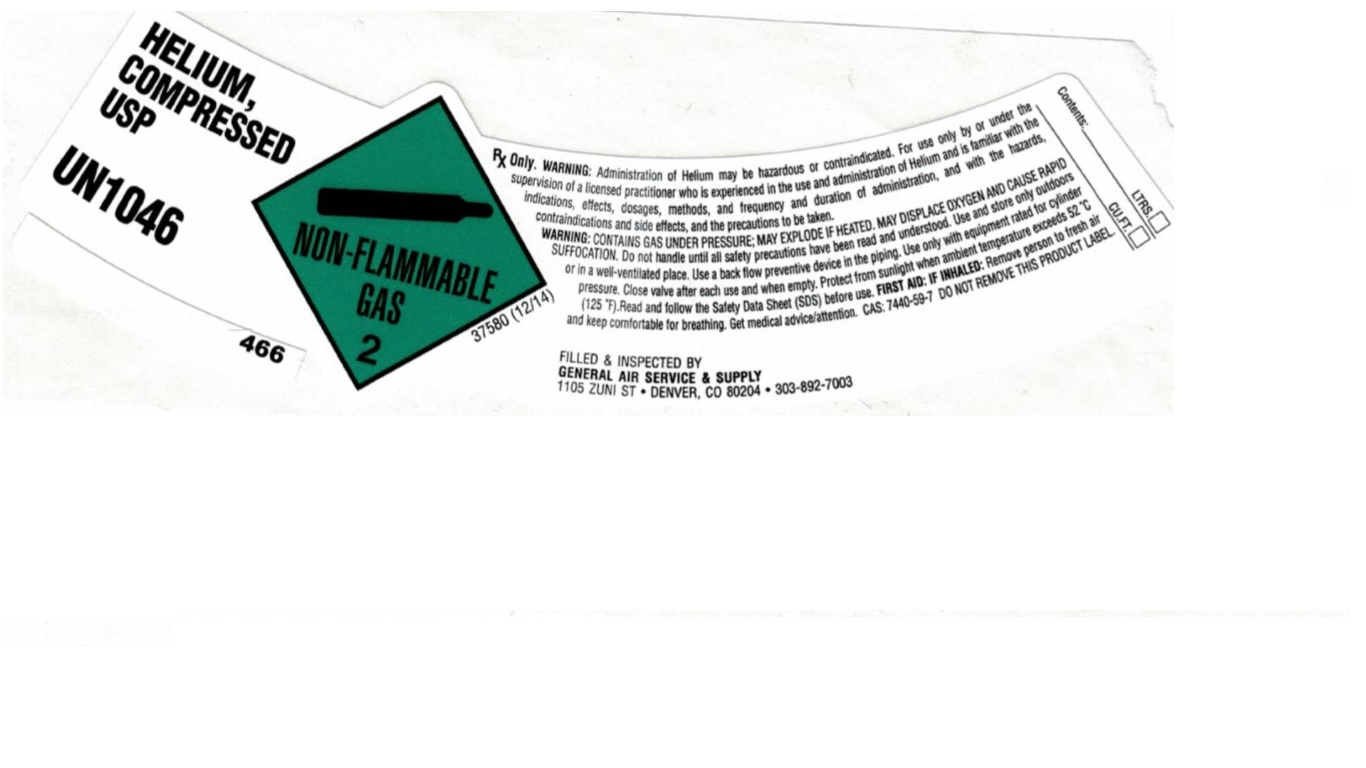 DRUG LABEL: Helium
NDC: 21220-200 | Form: GAS
Manufacturer: General Air Service & Supply Co
Category: prescription | Type: HUMAN PRESCRIPTION DRUG LABEL
Date: 20251126

ACTIVE INGREDIENTS: HELIUM 990 mL/1 L

Helium -200

PACKAGE LABEL

HELIUM, COMPRESSED USP
UN1046
Rx Only. WARNING: Administration of Helium may be hazardous or contraindicated. For use only by or under the supervision of a licensed practitioner who is experienced in the use and administration of Helium and is familiar with the indications, effects, dosages, methods, and frequency and duration of administration, and with the hazards, contraindications and side effects, and the precautions to be taken.
WARNING: CONTAINS GAS UNDER PRESSURE; MAY EXPLODE IF HEATED. MAY DISPLACE OXYGEN AND CUASE RAPID SUFFOCATION. Do not handle until all safety precautions have been read and understood. Use and store only outdoors or in a well-ventilated place Use a back flow preventive device in the piping. Use only with equipment rated for cylinder pressure. Close valve after each use and when empty. Protect from sunlight when ambient temperature exceeds 52 C (125 F). Read and follow the Safety Data Sheet (SDS) before use. FIRST AID: IF INHALED: Remove person to fresh air and keep comfortable for breathing. Get medical advice/attention. CAS: 7440-59-7 DO NOT REMOVE THIS PRODUCT LABEL.
FILLED & INSPECTED BY
GENERAL AIR SERVICE & SUPPLY
1105 ZUNI ST
DENVER, CO 80204
303-892-7003